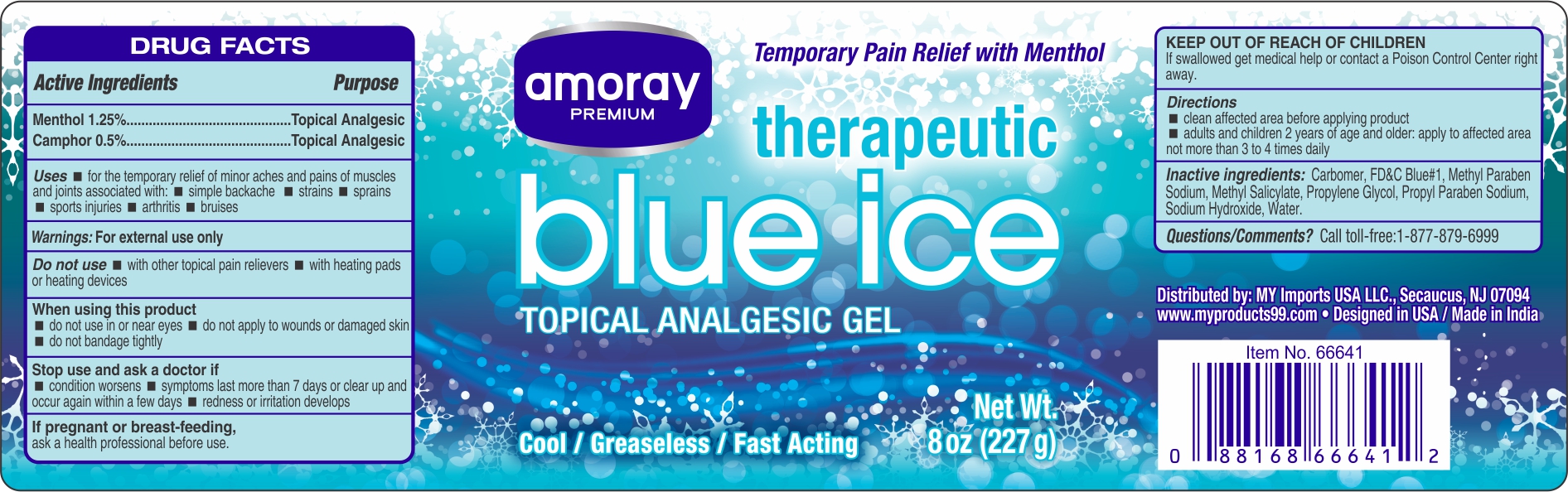 DRUG LABEL: AMORAY Analgesic  Gel
NDC: 51628-3021 | Form: GEL
Manufacturer: MY IMPORTS USA  LLC
Category: otc | Type: HUMAN OTC DRUG LABEL
Date: 20190503

ACTIVE INGREDIENTS: MENTHOL 1.25 g/100 g; CAMPHOR (SYNTHETIC) 0.5 g/100 g
INACTIVE INGREDIENTS: METHYLPARABEN SODIUM; CARBOXYPOLYMETHYLENE; FD&C BLUE NO. 1; WATER; SODIUM HYDROXIDE; PROPYLPARABEN SODIUM; PROPYLENE GLYCOL; METHYL SALICYLATE

AMORAY Ice Gel

Active Ingredients

Menthol 1.25 %

Camphor 0.5%

Purpose

Topical Analgesic

Uses:

- for temporary relief of minor aches and pains in muscles and joints associated with:
- simple backaches,
- strains
- sprains
- sports injuries
- arthritis
- bruises

Warnings

FOR EXTERNAL USE ONLY

Do not use:

- with other topical pain relievers
- with heating pads or heating devices

When using this product

- do not use in or near eyes
- do not apply to wounds or damaged skin
- do not bandage tightly

Stop use and ask a doctor if

- condition worsens
- symptoms last more than 7 days or clear up and occur again within a few days
- redness or irritation develops

If pregnant or breastfeeding

ask a health professional before use

KEEP OUT OF REACH OF CHILDREN

If swallowed get Medical Help or contact a Poison Control Center right away

Directions

- clean affected area before applying product
- adults and children 2 years of age and older; apply to affected area not more than 3 to 4 times daily

Inactive Ingredients

Carbomer, FD&C Blue No.1, Methyl Paraben Sodium, Methyl Salicylate, Propylene Glycol, Propyl Paraben Sodium, Sodium hydroxide, Water